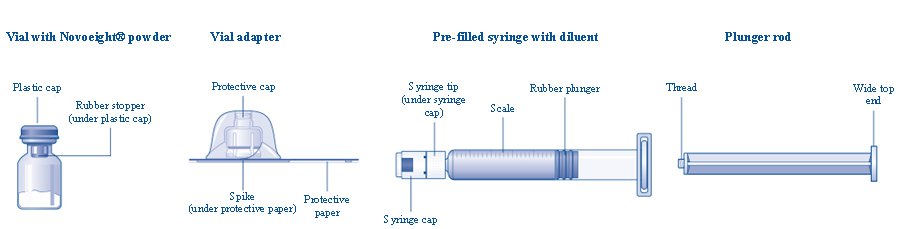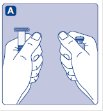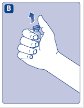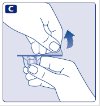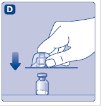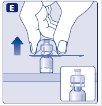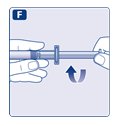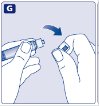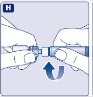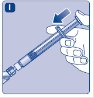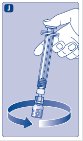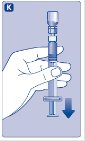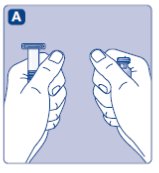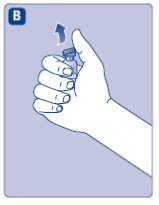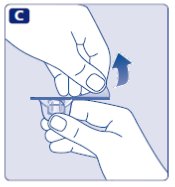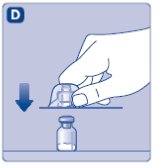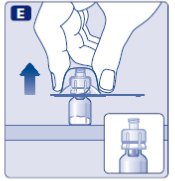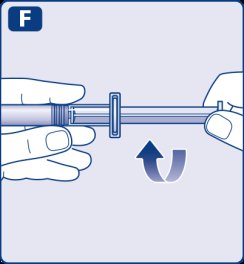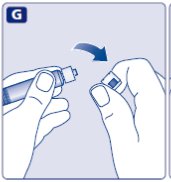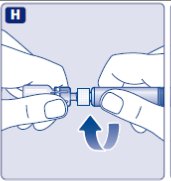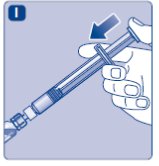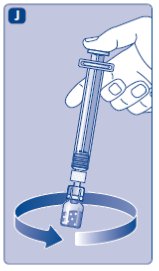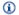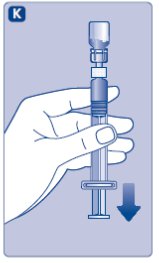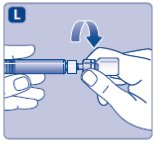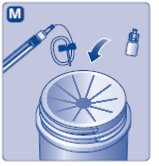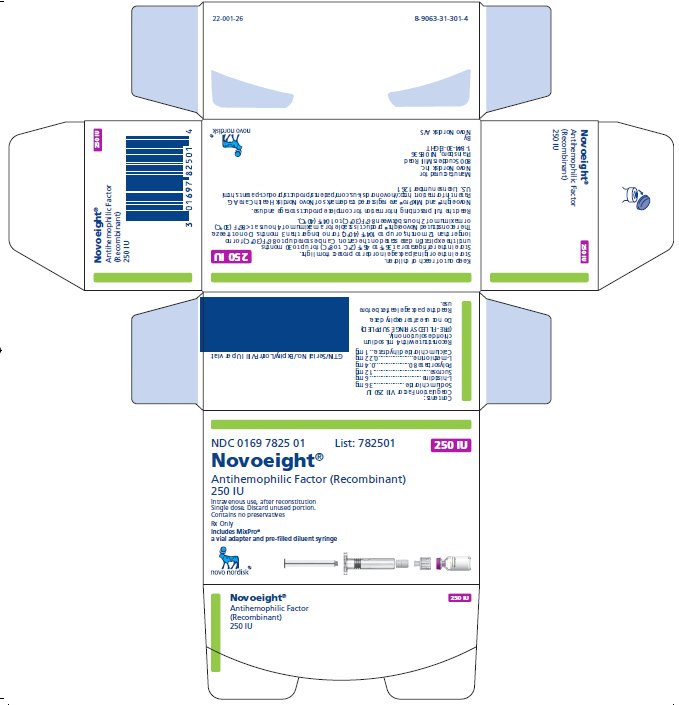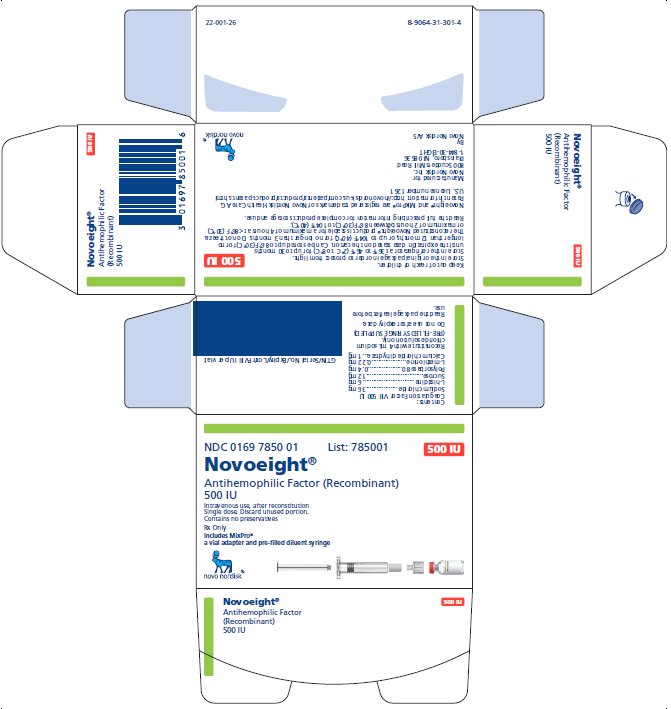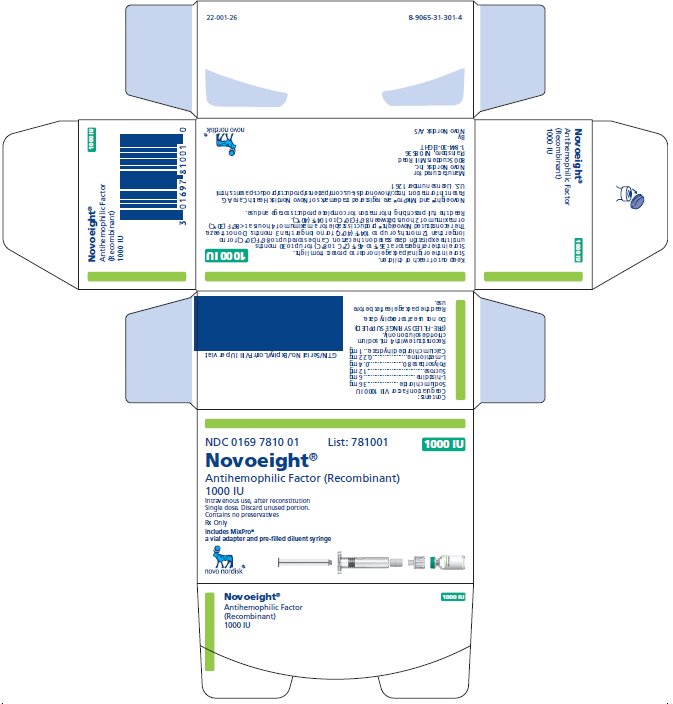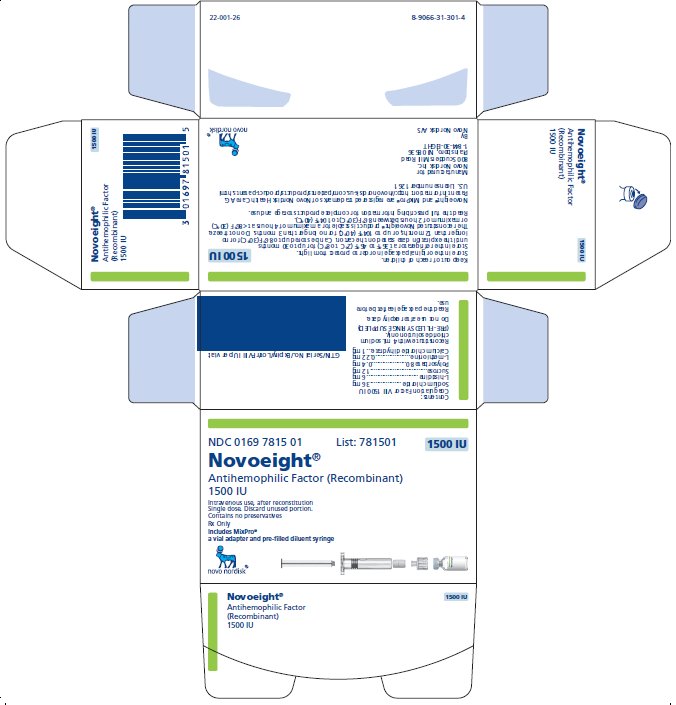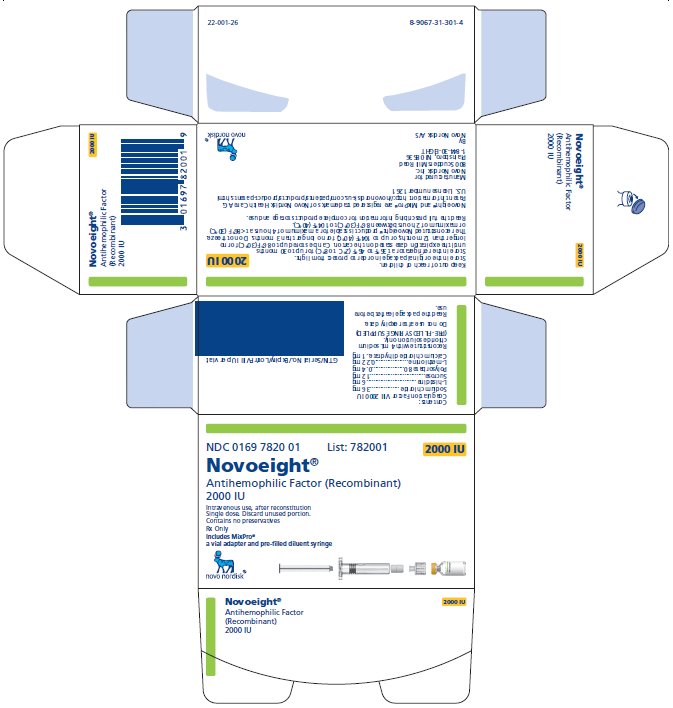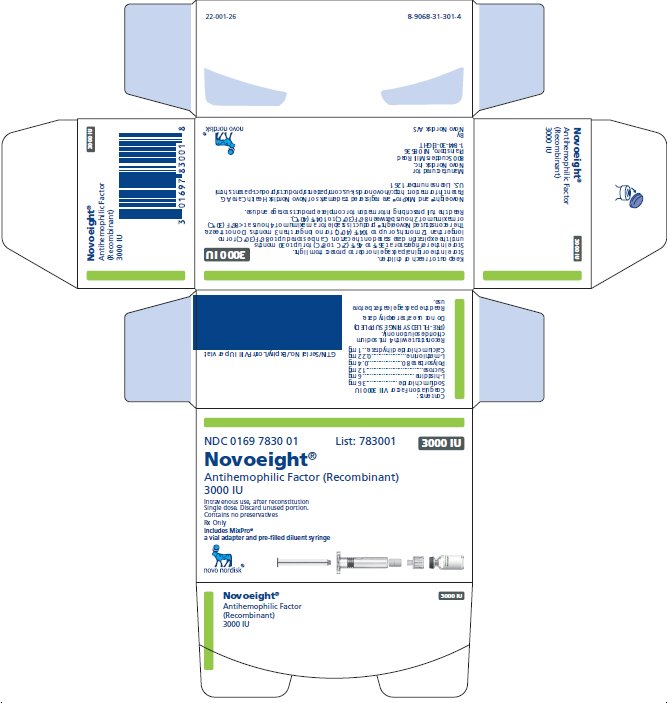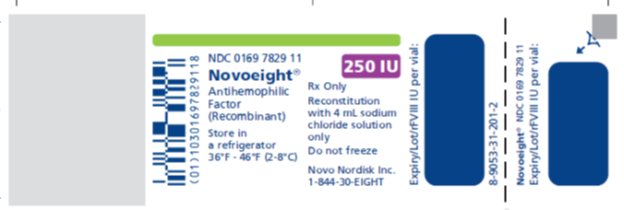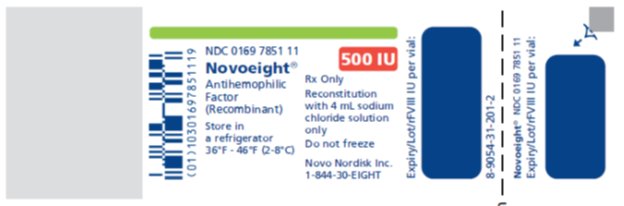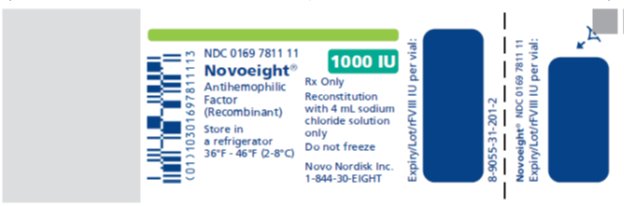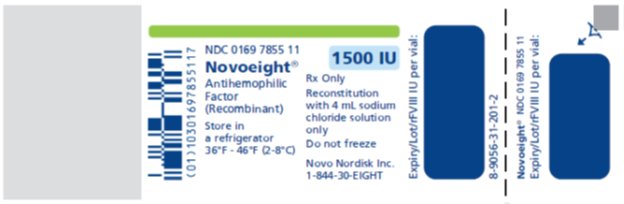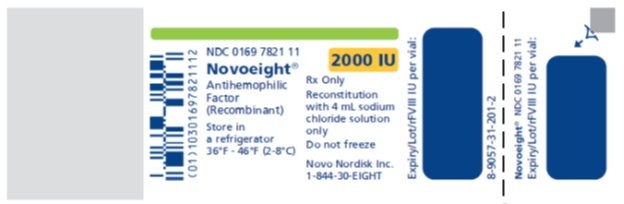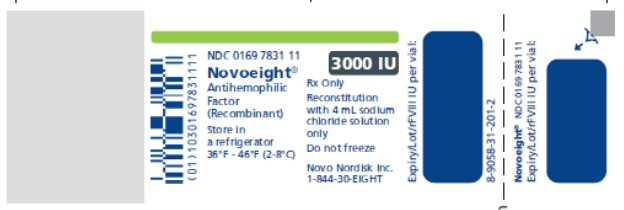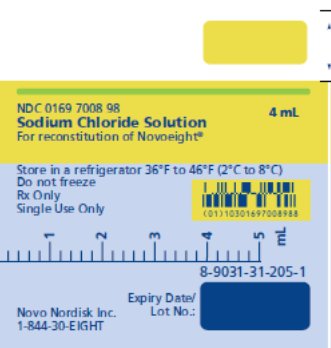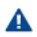 DRUG LABEL: NOVOEIGHT
NDC: 0169-7825 | Form: KIT | Route: INTRAVENOUS
Manufacturer: Novo Nordisk
Category: other | Type: PLASMA DERIVATIVE
Date: 20200731

ACTIVE INGREDIENTS: ANTIHEMOPHILIC FACTOR, HUMAN RECOMBINANT 62.5 [iU]/1 mL
INACTIVE INGREDIENTS: SODIUM CHLORIDE 18 mg/1 mL; HISTIDINE 1.5 mg/1 mL; SUCROSE 3 mg/1 mL; POLYSORBATE 80 0.1 mg/1 mL; METHIONINE 0.055 mg/1 mL; CALCIUM CHLORIDE 0.25 mg/1 mL; SODIUM CHLORIDE

HIGHLIGHTS OF PRESCRIBING INFORMATION

These highlights do not include all the information needed to use NOVOEIGHT safely and effectively. See full prescribing information for NOVOEIGHT.
NOVOEIGHT (antihemophilic factor, recombinant)
lyophilized powder for solution, for intravenous use
Initial U.S. Approval: 2013

1 INDICATIONS AND USAGE

Novoeight is an Antihemophilic Factor (Recombinant) indicated for use in adults and children with hemophilia A for:

- On-demand treatment and control of bleeding episodes
- Perioperative management
- Routine prophylaxis to reduce the frequency of bleeding episodes.

Novoeight is not indicated for the treatment of von Willebrand disease. (1)

2 DOSAGE AND ADMINISTRATION

For intravenous injection after reconstitution only (2)

- Each vial of Novoeight contains the labeled amount of recombinant Factor VIII in international units (IU). (2)
- The required dosage is determined using the following formula:
Dosage Required (IU) = Body Weight (kg) × Desired Factor VIII Increase (IU/dL or % normal) × 0.5 (IU/kg per IU/dL)
- Frequency of Novoeight administration is determined by the type of bleeding episode and the recommendation of the treating physician. (2.1)

3 DOSAGE FORMS AND STRENGTHS

Novoeight is available as a lyophilized powder in single-dose vials of 250, 500, 1000, 1500, 2000 and 3000 international units. (3)

4 CONTRAINDICATIONS

Do not use in patients who have had life-threatening hypersensitivity reactions, including anaphylaxis, to Novoeight or its components, including hamster proteins. (4)

5 WARNINGS AND PRECAUTIONS

- Anaphylaxis and severe hypersensitivity reactions are possible. Patients may develop hypersensitivity to hamster proteins, which are present in trace amounts in the product. Should symptoms occur, discontinue Novoeight and administer appropriate treatment. (5.1)
- Development of activity-neutralizing antibodies (inhibitors) may occur. If expected plasma factor VIII activity levels are not attained, or if bleeding is not controlled with an appropriate dose, perform an assay that measures factor VIII inhibitor concentration. (5.2, 5.3)

6 ADVERSE REACTIONS

The most frequently reported adverse reactions (≥ 1%) were inhibitors in Previously Untreated Patients (PUPs), injection site reactions, and pyrexia. (6)

To report SUSPECTED ADVERSE REACTIONS, contact Novo Nordisk Inc. at 1-844-303-4448 or FDA at 1-800-FDA-1088 or www.fda.gov/medwatch.

8 USE IN SPECIFIC POPULATIONS

- Pediatric Use: Clearance (based on per kg body weight) is higher in children. Higher or more frequent dosing may be needed. (8.4)
- Obesity: The area under the curve (AUC) is higher and clearance lower in adult patients with body mass index (BMI) ≥ 30 kg/m^2 than in patients with BMI < 30kg/m^2. Adjust dose as necessary. (8.6, 12.3)

FULL PRESCRIBING INFORMATION

1 INDICATIONS AND USAGE

Novoeight, Antihemophilic Factor (Recombinant), is a human antihemophilic factor (human blood coagulation

factor VIII (FVIII)) indicated for use in adults and children with hemophilia A for:

- On-demand treatment and control of bleeding episodes
- Perioperative management
- Routine prophylaxis to reduce the frequency of bleeding episodes

Novoeight is not indicated for the treatment of von Willebrand disease.

2 DOSAGE AND ADMINISTRATION

For intravenous injection after reconstitution only.

2.1 Dose

- Dosage and duration of treatment depend on the severity of the factor VIII deficiency, on the location and extent of bleeding, and the patient’s clinical condition. Careful monitoring of replacement therapy is necessary in cases of major surgery or life-threatening bleeding episodes.
- Each vial of Novoeight contains the labeled amount of recombinant factor VIII in international units (IU). One IU of factor VIII activity corresponds to the quantity of factor VIII in one milliliter of normal human plasma. The calculation of the required dosage of factor VIII is based on the empirical finding that one IU of factor VIII per kg body weight raises the plasma factor VIII activity by two IU/dL. This relationship causes a factor of 0.5 to be present in the dose calculation formula shown below.
- The required dosage can be determined using the following formula:
Dosage (IU) = Body Weight (kg) × Desired Factor VIII Increase (IU/dL or % normal) × 0.5

The final dose calculated is expressed as IU

- Base the dose and frequency of Novoeight on the individual clinical response. Patients may vary in their pharmacokinetic and clinical responses [See Clinical Pharmacology (12.3)].

On-demand Treatment and Control of Bleeding Episodes

A guide for dosing Novoeight for on-demand treatment and control of bleeding episodes is provided in Table 1. Dose to maintain a plasma factor VIII activity level at or above the plasma levels (in % of normal or in IU/dL) outlined in Table 1.

Table 1: Dosing for On-demand Treatment and Control of Bleeding Episodes

Type of Bleeding Episodes | Factor VIII Level Required (IU/dL or % of normal) | Frequency of Doses (hours) | Duration of Therapy (days)
Minor; Early hemarthrosis, minor muscle or oral bleeding | 20-40 | 12-24 | At least 1 day until bleeding resolution is achieved
Moderate; Muscle bleeding, bleeding into the oral cavity or mild head trauma | 30-60 | 12-24 | Until pain and acute disability are resolved (approximately 3-4 days)
Major; Life or limb threatening hemorrhage, Gastrointestinal bleeding, intracranial, intra-abdominal or intrathoracic bleeding, fractures | 60-100 | 8-24 | Until resolution of bleed (approximately 7-10 days)

Perioperative Management

A guide for dosing Novoeight during surgery (perioperative management) is provided in Table 2. Consider maintaining a plasma factor VIII activity level at or above the plasma levels (in % of normal or in IU/dL) outlined in Table 2.

Table 2: Dosing for Perioperative Management

Type of Surgery | Factor VIII Level Required (IU/dL or % of normal) | Frequency of Doses (hours) | Duration of Therapy (days)
Minor; Including tooth extraction | 30-60 | 24 | At least 1 day until healing is achieved
Major; Intracranial, intra-abdominal, intrathoracic, or joint replacement surgery | 80-100; (pre-and post-operative) | 8-24 | Until adequate wound healing, then continue therapy for at least 7 days to maintain a factor VIII activity of 30% to 60% (IU/dL)

Routine Prophylaxis

A guide for dosing Novoeight for routine prophylaxis is included below in Table 3.

Table 3: Dosing for Routine Prophylaxis

Patient Population | Factor VIII Dose Required (IU/kg) | Frequency of Doses
Adults and adolescents (≥ 12 years) | 20-50 | 3 times weekly
Adults and adolescents (≥ 12 years) | 20-40 | Every other day
Children (<12 years) | 25-60 | 3 times weekly
Children (<12 years) | 25-50 | Every other day

2.2 Preparation and Reconstitution

- Always wash hands and ensure that the area is clean before performing the procedures.
- Use aseptic technique during the reconstitution procedures.
- If the dose requires more than one vial of Novoeight per injection, reconstitute each vial according to the following instructions:

Overview of Novoeight Package

Reconstitution

1. Bring the Novoeight vial and the pre-filled diluent syringe to room temperature.
2. Remove the plastic cap from the Novoeight vial.
3. Wipe the rubber stopper on the vial with a sterile alcohol swab and allow it to dry prior to use.
4. Remove the protective paper from the vial adapter. Do not remove the vial adapter from the protective cap.
5. Place the vial on a flat and solid surface. While holding the protective cap, place the vial adapter over the Novoeight vial and press down firmly on the protective cap until the vial adapter spike penetrates the rubber stopper.
6. Carefully remove the protective cap from the vial adapter.
7. Grasp the plunger rod as shown in the diagram. Attach the plunger rod to the syringe by holding the plunger rod by the wide top end. Turn the plunger rod clockwise into the rubber plunger inside the pre-filled diluent syringe until resistance is felt.

8. Break off the syringe cap from the pre-filled diluent syringe by snapping the perforation of the cap.
9. Connect the pre-filled diluent syringe to the vial adapter by turning it clockwise until it is secured.
10. Push the plunger rod to slowly inject all the diluent into the vial.
11. Without removing the syringe, gently swirl the Novoeight vial until all of the powder is dissolved.
12. Use the Novoeight solution immediately. If not, store the solution in the vial with the vial adapter and the syringe attached. Use Novoeight within 4 hours after reconstitution when stored at <86°F (30°C) or within 2 hours when stored between 86°F (30°C) to 104°F (40°C).

2.3 Administration

For intravenous injection only.

- Inspect the reconstituted Novoeight solution visually for particulate matter and discoloration prior to administration, whenever solution and container permit. Do not use if particulate matter or discoloration is observed.
- Do not administer Novoeight in the same tubing or container with other medicinal products.
1. Invert the Novoeight vial and slowly draw the solution into the syringe.
2. Detach the syringe from the vial adapter by turning the syringe counterclockwise.
3. Attach the syringe to the luer end of an infusion needle set.
4. Inject the reconstituted Novoeight intravenously slowly over 2 to 5 minutes.
5. After injection, safely dispose of the syringe with the infusion set, the vial with the vial adapter, any unused Novoeight and other waste materials. Accidental needle stick with a needle contaminated with blood can transmit infectious viruses including HIV (AIDS) and hepatitis. Obtain immediate medical attention if injury occurs. Place needles in a sharps container after single-use.

Caution:

The pre-filled diluent syringe is made of glass with an internal tip diameter of 0.037 inches, and is compatible with a standard Luer-lock connector.

Some needleless connectors for intravenous catheters are incompatible with the glass diluent syringes (for example, certain connectors with an internal spike, such as Clave® /MicroClave®, InVision-Plus®, InVision-Plus CS®, Invision-Plus Junior®, Bionector®), and their use can damage the connector and affect administration. To administer Novoeight through incompatible needleless connectors, withdraw the reconstituted product into a standard 10 mL sterile Luer-lock plastic syringe.

3 DOSAGE FORMS AND STRENGTHS

Novoeight is available as a white lyophilized powder in single-dose vials containing 250, 500, 1000, 1500, 2000 and 3000 international units per vial.

After reconstitution with 4 mL of 0.9% sodium chloride solution, each mL of reconstituted solution contains approximately 62.5, 125, 250, 375, 500 or 750 international units of Novoeight, respectively.

4 CONTRAINDICATIONS

Novoeight is contraindicated in patients who have had life-threatening hypersensitivity reactions, including anaphylaxis, to Novoeight or its components (including traces of hamster proteins).

5 WARNINGS AND PRECAUTIONS

5.1 Hypersensitivity Reactions

Hypersensitivity reactions, including anaphylaxis, are possible with Novoeight. Novoeight contains trace amounts of hamster proteins. Patients treated with this product may develop hypersensitivity to these non-human mammalian proteins. Early signs of hypersensitivity reactions that can progress to anaphylaxis include angioedema, chest tightness, dyspnea, wheezing, urticaria, and pruritus. Immediately discontinue administration and initiate appropriate treatment if allergic- or anaphylactic-type reactions occur.

5.2 Neutralizing Antibodies

Formation of neutralizing antibodies (inhibitors) to factor VIII can occur following administration of Novoeight. Previously untreated patients (PUPs) are at greatest risk for inhibitor development with all factor VIII products. Inhibitors have been reported following administration of Novoeight in PUPs [see Adverse Reactions (6.1)]. Monitor all patients for the development of inhibitors by appropriate clinical observation and laboratory testing. If the expected plasma levels of factor VIII activity are not attained, or if bleeding is not controlled with an appropriate dose, perform testing for factor VIII inhibitors.

5.3 Monitoring Laboratory Tests

- Monitor plasma factor VIII activity levels by the one-stage clotting assay or the chromogenic substrate assay to confirm that adequate factor VIII levels have been achieved and maintained, when clinically indicated. [See Dosage and Administration (2.1)]
- Perform assay to determine if factor VIII inhibitor is present if expected plasma factor VIII activity levels are not attained, or if bleeding is not controlled with the expected dose of Novoeight. Determine inhibitor levels in Bethesda Units.

6 ADVERSE REACTIONS

The most frequently reported adverse reactions observed in clinical trials (≥ 1%) were injection site reactions, and pyrexia.

6.1 Clinical Trials Experience

Because clinical trials are conducted under widely varying conditions, adverse reaction rates observed in the clinical trials of a drug cannot be directly compared to rates in clinical trials of another drug and may not reflect the rates observed in clinical practice.

During the clinical development of Novoeight, 301 male patients (242 previously treated patients (PTPs); exposed to a factor VIII-containing product for ≥150 days and 59 Previously Untreated Patients (PUPs)) with severe hemophilia A (factor VIII level ≤1%) received at least one dose of Novoeight as part of either routine prophylaxis, on-demand treatment of bleeding episodes, perioperative management of major and minor surgical, dental, or other invasive procedures, Immune Tolerance Induction (ITI) or pharmacokinetic evaluation of Novoeight with more than 140,000 exposure days (corresponding to over 900 patient years). During prophylaxis treatment subjects received a median of 468 injections of Novoeight (range 1-1317).

Table 4: Summary of Adverse Reactions (ARs) with a Frequency ≥ 1% in 301 Subjects

MedDRA System Organ class | Adverse Reactions | Frequency N (%)
General disorders and administration site conditions | Pyrexia | 3 (1.0%)
General disorders and administration site conditions | Injection site reaction | 3 (1.0%)

Immunogenicity

Subjects were monitored for neutralizing antibodies to factor VIII and binding antibodies to CHO and murine protein. No PTPs developed confirmed neutralizing antibodies to factor VIII. One twenty-two month old previously treated child had a positive neutralizing antibody to factor VIII of 1.3 [BU] in the Bethesda assay after 15 exposure days that was not confirmed when checked after 20 exposure days. In vivo recovery was normal for this child and no clinical adverse findings were observed. In the completed main phase of the clinical trial in PUPs, 24 of 56 (42.9%) patients developed inhibitors with a mean of 14.1 exposure days at the time of the first positive inhibitor test; 15 (26.8%) PUPs developed high titer (≥ 5 BU) inhibitors. High risk genetic mutations were identified in 91.7% of the overall inhibitors and 93.3% of the high titer inhibitors.

No patients developed de novo anti-murine antibodies. Nineteen subjects were positive for anti-Chinese hamster ovary (CHO) cell protein antibodies. Two of these subjects changed from anti-CHO negative to anti-CHO positive and 6 subjects changed from anti-CHO positive to anti-CHO negative. The remaining 11 subjects were either positive throughout the trials (n=6), negative at baseline and end-of trial but with transient positive samples (n=2), or positive at baseline and end-of trial but with negative samples in between (n=3). No clinical adverse findings were observed in any of these subjects.

The detection of antibody formation is highly dependent on the sensitivity and specificity of the assay. Additionally, the observed incidence of antibody (including neutralizing antibody) positivity in an assay may be influenced by several factors, including assay methodology, sample handling, timing of sample collection, concomitant medications, and underlying disease. For these reasons, it may be misleading to compare the incidence of antibodies to Novoeight with the incidence of antibodies to other products.

6.2 Postmarketing Experience

Adverse reactions reported during post marketing period were similar in nature to those observed during clinical trials.

8 USE IN SPECIFIC POPULATIONS

8.1 Pregnancy

Risk Summary

As hemophilia mainly affects males, there are no adequate and well-controlled studies using Novoeight in pregnant women to determine whether there is a drug-associated risk. Animal reproduction studies have not been conducted with Novoeight.

In the U.S. general population, the estimated background risk of major birth defect and miscarriage in clinically recognized pregnancies is 2-4% and 15-20%, respectively. There is no reliable data on the incidences specific to the hemophilia A population.

8.2 Lactation

Risk Summary

There is no information regarding the presence of Novoeight in human milk, the effect on the breastfed infant, and the effects on milk production. The developmental and health benefits of breastfeeding should be considered along with the mother’s clinical need for Novoeight and any potential adverse effects on the breastfed infant from Novoeight or from the underlying maternal condition.

8.4 Pediatric Use

Children have shorter half-life and lower recovery of factor VIII than adults. Because clearance (based on per kg body weight) has been demonstrated to be higher in the pediatric population, higher or more frequent dosing based on body weight may be needed. [See Clinical Pharmacology (12.3)]

Safety and efficacy studies have been performed in 146 pediatric patients <18 years of age. Ninety (including all 59 PUPs) of these subjects (62%) were <6 years of age, 32 (22%) were 6 to <12 years of age, and 24 (16%) were adolescents (12 to <18 years of age). Subjects during routine prophylaxis and treatment of bleeds received Novoeight at the dose levels described in Tables 1 and 3. A total of 1290 bleeds in 127 subjects were treated with Novoeight. The majority of the bleeds 1162 (90%) were of mild/moderate severity. Of these 1290 bleeds, 1140 (88%) were rated excellent or good in their response to treatment with Novoeight and in 17 (1%) the response to treatment was unknown. A total of 1100 (85%) of the bleeds were resolved with one or two injections of Novoeight. Routine prophylactic treatment has been shown to reduce joint bleeding. [See Clinical Studies (14)]

8.5 Geriatric Use

Clinical studies of Novoeight did not include sufficient numbers of patients aged 65 and over to determine whether they respond differently from younger patients.

8.6 Obesity

In the extension trial, in six adult patients with body mass index (BMI) ≥ 30 kg/m^2, the AUC was higher and clearance lower than in patients with BMI < 30 kg/m^2. There is insufficient data to recommend specific dose adjustments for patients with BMI ≥ 30 kg/m^2. Adjust dose as necessary and per prescriber’s discretion for patients with BMI ≥ 30 kg/m^2. [See Clinical Pharmacology (12.3)].

11 DESCRIPTION

Novoeight is formulated as a sterile, non-pyrogenic, lyophilized powder for intravenous injection after reconstitution with the diluent (0.9% sodium chloride). Novoeight is available in single-dose vials that contain nominally 250, 500, 1000, 1500, 2000 or 3000 international units (IU) per vial. When reconstituted with the appropriate volume of diluent, the product contains the following components per mL: 18 mg sodium chloride, 1.5 mg L-histidine, 3 mg sucrose, 0.1 mg polysorbate 80, 0.055 mg L-methionine and 0.25 mg calcium chloride dihydrate. The product contains no preservative. Each vial of Novoeight is labeled with the actual rFVIII activity expressed in IU determined by the one-stage clotting assay, using a reference material calibrated against a World Health Organization (WHO) International Standard for FVIII Concentrates. One IU, as defined by the WHO standard for human FVIII, is approximately equal to the level of FVIII activity in 1 mL of fresh pooled human plasma. The specific activity of Novoeight is approximately 8340 IU per milligram of protein.

The active ingredient in Novoeight is a recombinant (r) analogue of human coagulation factor VIII (FVIII) with a molecular mass of 166 kDa, calculated excluding post-translational modifications. The rFVIII molecule in Novoeight is a glycoprotein containing a heavy chain and a light chain, with 21 of the 908 amino acids of the B-domain of endogenous FVIII connected to the C-terminus of the heavy chain. Once activated, the resulting rFVIIIa has a comparable structure to the endogenous FVIIIa.

Novoeight is synthesized by a genetically engineered Chinese hamster ovary (CHO) cell line which secretes rFVIII into the cell culture medium. The rFVIII protein is purified using a series of chromatography steps, one of which is the use of an immunoaffinity column in which a monoclonal antibody, produced in CHO cells and directed against FVIII, is employed to selectively isolate the rFVIII from the medium. The production process includes two dedicated viral clearance steps - a detergent treatment step for inactivation and a 20-nm filtration step for removal of viruses. No additives of human or animal origin are used in the cell culture, purification and formulation of Novoeight.

12 CLINICAL PHARMACOLOGY

12.1 Mechanism of Action

Novoeight temporarily replaces the missing clotting factor VIII that is needed for effective hemostasis.

12.2 Pharmacodynamics

The activated partial thromboplastin time (aPTT) is prolonged in patients with hemophilia A. Determination of aPTT is a conventional in vitro assay for the biological activity of FVIII. Treatment with Novoeight normalizes the aPTT over the effective dosing period.

12.3 Pharmacokinetics

All pharmacokinetic studies with Novoeight were conducted in previously treated patients with severe hemophilia A (factor VIII ≤ 1%). Analysis of plasma samples was conducted using both the one-stage clotting assay and the chromogenic assay.

In a multi-center, multi-national, open-label, single dose pharmacokinetic study, 23 patients with severe hemophilia A received 50 international units/kg of Novoeight intravenously. Two patients were below the age of 18 years (13 and 17 years). The pharmacokinetic parameters for 20 patients who completed the study are summarized in Table 5.

Table 5: Pharmacokinetics of Novoeight in 20 adult and adolescent patients with hemophilia Aa

Parameters | Clotting Assay | Chromogenic Assay
Parameters | Mean (SD) | Mean (SD)
Incremental Recovery (IU/mL)/(IU/kg) | 0.020 (0.002) | 0.028 (0.006)
AUC (IU*h/mL) | 14.2 (3.8) | 18.7 (5.1)
CL (mL/h/kg) | 3.74 (0.95) | 2.87 (0.80)
t½ (h) | 10.8 (4.9) | 12.0 (9.3)
Vss (mL/kg) | 53.4 (10.9) | 44.3 (28.2)
Cmax (IU/mL) | 1.07 (0.16) | 1.54 (0.29)
MRT (h) | 15.4 (6.4) | 16.4 (10.1)

aDose: 50 IU/kg turoctocog alfa (single i.v. dose)

In a single dose PK assessment in adult patients with BMI ≥ 30 kg/m^2 in the extension trial [See Clinical Studies (14)], the AUC was 59% higher and clearance was 33% lower in 6 subjects with BMI ≥ 30 kg/m^2 compared to subjects with normal BMI, see Table 6.

Table 6: Pharmacokinetics of Novoeight in 6 adult patients with BMI ≥ 30 kg/m2a

Parameters | Clotting Assay | Chromogenic Assay
Parameters | Mean (SD) | Mean (SD)
BMI (kg/m^2) | 33.35 (2.367); Range 30.5 – 37.2
Incremental Recovery (IU/mL)/(IU/kg) | 0.024 (0.01) | 0.035 (0.01)
AUC (IU*h/mL) | 22.64 (5.74) | 31.02 (9.78)
CL (mL/h/kg) | 2.49 (0.77) | 1.94 (0.95)
t½ (h) | 12.80 (2.99) | 12.40 (3.16)
Vss (mL/kg) | 39.67 (10.03) | 29.79 (7.87)
Cmax (IU/mL) | 1.49 (0.36) | 2.03 (0.51)
MRT (h) | 16.84 (4.78) | 16.58 (4.26)

aDose: 50 IU/kg turoctocog alfa (single i.v. dose)

In a separate pharmacokinetic study, 28 pediatric patients with severe hemophilia A (14 patients were below 6 years of age and 14 patients were between 6 to <12 years of age) received a single dose of 50 international units/kg Novoeight. The pharmacokinetic parameters of Novoeight are summarized in Table 7 for both age groups.

Table 7: Pharmacokinetics of Novoeight in 28 pediatric patients with hemophilia A

Parameters | Clotting Assay |  | Chromogenic Assay
Parameters | 0 to <6 years | 6 to <12 years | 0 to <6 years | 6 to <12 years
 | Mean (SD) |  | Mean (SD)
Incremental Recovery (IU/mL)/(IU/kg) | 0.018 (0.007) | 0.020 (0.004) | 0.022 (0.006) | 0.025 (0.006)
AUC (IU*h/mL) | 9.9 (4.1) | 11.1 (3.7) | 12.2 (4.4) | 14.4 (3.5)
CL (mL/h/kg) | 6.26 (3.73) | 5.02 (1.67) | 4.60 (1.75) | 3.70 (1.00)
t½ (h) | 7.7 (1.8) | 8.0 (1.9) | 10.0 (1.7) | 9.4 (1.5)
Vss (mL/kg) | 57.3 (26.8) | 46.8 (10.6) | 55.8 (23.7) | 41.2 (6.0)
Cmax (IU/mL) | 1.00 (0.58) | 1.07 (0.35) | 1.12 (0.31) | 1.25 (0.27)
MRT (h) | 9.7 (2.5) | 9.9 (2.6) | 12.1 (1.9) | 11.6 (2.3)

The pharmacokinetic parameters were comparable between younger (0 to < 6 years) and older (6 to < 12 years) children. The mean clearance of Novoeight in younger and older children was 67% and 34% higher (based on per kg body weight) than in adults (3.74 mL/h/kg) when using the clotting assay, and 60% and 29% higher than in adults (2.87 mL/h/kg) when using the chromogenic assay. The mean half-life of Novoeight in younger and older children was 29% and 26% shorter than in adults (10.8 hours) when using the clotting assay, and 16% and 21% shorter than in adults (12 hours) when using the chromogenic assay.

13 NONCLINICAL TOXICOLOGY

13.1 Carcinogenesis, Mutagenesis, Impairment of Fertility

Long-term studies in animals to evaluate the carcinogenic potential of Novoeight, or studies to determine the effects of Novoeight on genotoxicity or fertility have not been performed. An assessment of the carcinogenic potential of Novoeight was completed, and no carcinogenic risk from product use has been identified.

14 CLINICAL STUDIES

Four multi-center, open-label, non-controlled trials have been conducted to evaluate the safety and efficacy of Novoeight in the on-demand treatment and control of breakthrough bleeds, routine prophylaxis and perioperative management in patients with hemophilia A. Three of these trials were performed in PTPs (two trials and one extension trial) and the fourth in PUPs. The analysis included 297 exposed subjects: 175 previously treated adolescents or adult subjects from the age of 12 years (≥150 exposure days), 63 previously treated pediatric subjects below the age of 12 years (≥50 exposure days) and 59 PUPs below 6 years of age. Immunocompetent patients with severe hemophilia A (factor VIII activity ≤1%) and no history of FVIII inhibitors were eligible for the trials. Subjects during routine prophylaxis and treatment of bleeds received Novoeight at the dose levels described in Tables 1 and 3. Breakthrough bleeds were treated at the investigator’s discretion aiming for a FVIII activity level above 0.5 IU/mL. Treatment during surgery was at the investigator’s discretion aiming for a FVIII trough activity level above 0.5 IU/mL.

On-demand Treatment and Control of Bleeding Episodes

A total of 3153 bleeds in 260 subjects were treated with Novoeight. The majority of the bleeds (90%) were of mild/moderate severity, 54% of the bleeds were spontaneous and 67% of the bleeds were localized in joints.

An overall assessment of efficacy was performed by the subject (for home treatment) or study site investigator (for treatment under medical supervision) using a four-point scale of excellent, good, moderate, or none. If the hemostatic response was rated as “excellent” or “good”, the treatment of the bleed was considered a success. If the hemostatic response was rated as “moderate or none” the treatment was considered a failure. Of these 3,153 bleeds, 2,809 (89%) were rated excellent or good in their response to treatment with Novoeight, 274 (9%) were rated as moderate, 25 (0.8%) were rated as having no response and for 45 (1%) the response to treatment was unknown. A total of 2,794 (89%) of the bleeds were resolved with one or two injections of Novoeight.

Of the 238 PTPs, 206 patients experienced 2,793 bleeds of which 2,492 (89%) were rated excellent or good in their response to treatment with Novoeight, 244 (9%) were moderate, 23 (0.8%) were rated as having no response, and for 34 (1%) the response to treatment was unknown. Of the 2,793 reported bleeds observed in 206 of the patients, 2,504 (90%) of the bleeds were resolved with 1–2 injections of Novoeight. The majority of the bleeds were of mild/moderate severity.

Of the 59 PUPs, 54 patients experienced 360 bleeds of which 317 (88%) were rated excellent or good in their response to treatment with Novoeight, 30 (8%) were moderate, 2 (0.6%) were rated as having no response, and for 11 (3%) the response to treatment was unknown. Of the 360 reported bleeds observed in 54 of the patients, 290 (81%) of the bleeds were resolved with 1–2 injections of Novoeight. The majority of the bleeds were of mild/moderate severity and the most frequent bleeds were subcutaneous.

Routine Prophylaxis

In the two trials, one trial including 150 adult/adolescent subjects (6 months duration) and the other trial including 63 pediatric subjects (4 months duration) received Novoeight for routine prophylaxis (Table 8). These previously treated patients received prophylaxis treatment every other day or three times weekly at the dose levels described in Table 3.

Table 8: Annualized Bleeding Rate (ABRa) for previously treated patients from the two trials

 | Small children; 0 - <6 years | Older children; 6 - <12 years | Adolescents; 12 - <18 years | Adults; ≥18 years | Total
Nb | 31 | 32 | 24 | 126 | 213
Median (IQR) | 2.97 (6.30) | 3.65 (8.93) | 3.98 (6.21) | 3.70 (9.02) | 3.67 (8.70)
Mean (95%CI) | 4.77 (3.07; 7.41) | 5.93 (3.81; 9.22) | 5.48 (3.29; 9.14) | 6.69 (5.36; 8.36) | 6.24 (5.25; 7.41)

a: The ABRs were estimated using a Poisson model allowing for overdispersion.

b: Patients dosed every other day or three times weekly

Abbreviations: N: number of patients; IQR: interquartile range defined as the difference between the 75th percentile and the 25th percentile; CI: confidence interval.

One hundred and eighty-eight (188) subjects from the two trials above continued into the extension trial (up to 6 years duration) (Table 9). Additionally, 18 subjects (7 subjects from an on-demand sub-trial and 11 subjects from a pharmacokinetic trial) were included in the extension trial. These previously treated patients received prophylaxis treatment every other day or three times weekly at the dose levels described in Table 3.

Table 9: Annualized Bleeding Rate (ABRa) for previously treated patients from the extension trial

 | Small children; 0 - <6 years | Older children; 6 - <12 years | Adolescents; 12 - <18 years | Adults; ≥18 years | Total
Nb | 27 | 28 | 23 | 128 | 206
Median (IQR) | 1.08 (2.83) | 1.57 (3.82) | 1.57 (2.34) | 1.38 (2.96) | 1.39 (2.94)
Mean (95%CI) | 1.87 (1.14; 3.09) | 2.90 (2.01; 4.17) | 1.93 (1.33; 2.82) | 2.61 (2.08; 3.28) | 2.45 (2.07; 2.90)

a: The ABRs were estimated using a Poisson model allowing for overdispersion.

b: Patients dosed every other day or three times weekly

Abbreviations: N: number of patients; IQR: interquartile range defined as the difference between the 75th percentile and the 25th percentile; CI: confidence interval.

In the trial with previously untreated patients, 56 subjects below 6 years of age received Novoeight for routine prophylaxis. The median annualized bleeding rate in the previously untreated patients was 2.9 (IQR 5.4) and the mean (95%CI) was 4.4 (3.3; 5.8).

Perioperative Management

A total of 30 surgeries were performed in 25 previously treated subjects between 8 and 58 years of age, of which 26 were major surgeries (20 orthopaedic, 5 non-orthopaedic and a circumcision), and 4 were minor (2 dental, 1 circumcision and 1 insertion of port-a-cath).

The investigator’s ratings of intra- and post-operative quality of hemostasis for these subjects were “excellent” or “good” for all cases.

16 HOW SUPPLIED/STORAGE AND HANDLING

How Supplied

- Novoeight is supplied in packages comprised of a single-dose vial containing nominally 250, 500, 1000, 1500, 2000, or 3000 international units (IU) of FVIII potency, a MixPro® pre-filled diluent syringe containing 0.9% sodium chloride solution, and sterile vial adapter with 25 micrometer filter, which serves as a needleless reconstitution device.
- The actual amount of FVIII potency in IU is stated on each carton and vial.

Presentation (Nominal Product Strength) | Carton NDC Number | Components
250 International Units | NDC 0169 7825 01 | - Novoeight in single-dose vial [NDC 0169-7829-11] - Pre-filled sodium chloride diluent in syringe, 4 mL [NDC 0169-7008-98] - Vial adapter
500 International Units | NDC 0169 7850 01 | - Novoeight in single-dose vial [NDC 0169-7851-11] - Pre-filled sodium chloride diluent in syringe, 4 mL [NDC 0169-7008-98] - Vial adapter
1000 International Units | NDC 0169 7810 01 | - Novoeight in single-dose vial [NDC 0169-7811-11] - Pre-filled sodium chloride diluent in syringe, 4 mL [NDC 0169-7008-98] - Vial adapter
1500 International Units | NDC 0169 7815 01 | - Novoeight in single-dose vial [NDC 0169-7855-11] - Pre-filled sodium chloride diluent in syringe, 4 mL [NDC 0169-7008-98] - Vial adapter
2000 International Units | NDC 0169 7820 01 | - Novoeight in single-dose vial [NDC 0169-7821-11] - Pre-filled sodium chloride diluent in syringe, 4 mL [NDC 0169-7008-98] - Vial adapter
3000 International Units | NDC 0169 7830 01 | - Novoeight in single-dose vial [NDC 0169-7831-11] - Pre-filled sodium chloride diluent in syringe, 4 mL [NDC 0169-7008-98] - Vial adapter

- The Novoeight vials are made of glass, closed with a chlorobutyl rubber stopper not made with natural rubber latex, and sealed with an aluminum cap.
- The pre-filled diluent syringes are made of glass, with a siliconised bromobutyl rubber plunger not made with natural rubber latex.
- The closed vials and pre-filled diluent syringes are equipped with a tamper-evident snap-off cap which is made of polypropylene.

Storage and Handling

- Store Novoeight in the original package in order to protect from light.
- Store Novoeight under refrigeration at a temperature of 36°F to 46°F (2°C to 8°C) for up to 30 months from the date of manufacture until the expiration date stated on the carton. During the 30-month shelf life, Novoeight may be kept at room temperature:
- up to 86°F (≤30°C) for no longer than 12 months
or
- up to 104°F(≤40°C) for no longer than 3 months
- Clearly record the date when the product was removed from the refrigerator in the space provided on the outer carton. Do not return the product to the refrigerator. Do not freeze Novoeight.
- Use Novoeight within 4 hours after reconstitution when stored at <86°F (30°C) or within 2 hours when stored between 86°F (30°C) to 104°F (40°C). Store the reconstituted product in the vial.
- Discard any unused reconstituted product.

17 PATIENT COUNSELING INFORMATION

- Advise patients to read the FDA-approved patient labeling (Patient Information and Instructions for Use).
- Allergic-type hypersensitivity reactions or anaphylaxis are possible with use of Novoeight. Inform patients of the early signs of hypersensitivity reactions including rash, hives, itching, facial swelling, tightness of the chest and wheezing. Advise patients to discontinue use of Novoeight immediately and contact their physician, and go to the emergency department if these symptoms occur.
- Advise patients to contact their physician or treatment facility for further treatment and/or assessment if they experience a lack of a clinical response to factor VIII replacement therapy, as this may be a manifestation of an inhibitor.
- Advise patients to consult with their healthcare provider prior to traveling. While traveling, patients should be advised to bring an adequate supply of Novoeight based on their current treatment regimen.

Version: 8

License Number: 1261

Novoeight® and MixPro® are registered trademarks of Novo Nordisk Health Care AG.

Patent Information: http://novonordisk-us.com/patients/products/product-patents.html

Clave® and MicroClave® are registered trademarks of ICU Medical Inc.

InVision-Plus®, InVision-Plus CS®, Invision-Plus® Junior® are registered trademarks of RyMed Technologies, Inc.

Bionector® is a registered trademark of Vygon.

© 2020 Novo Nordisk

For information contact:

Novo Nordisk Inc.

800 Scudders Mill Road

Plainsboro, NJ 08536, USA

1-844-30-EIGHT

Manufactured by:

Novo Nordisk A/S

Novo Allé, DK-2880 Bagsvaerd

FDA approved Patient Labeling

Patient Product Information

Novoeight® (NŌ-vō-eyt)

Antihemophilic Factor (Recombinant)

Read the Patient Product Information and the Instructions For Use that come with Novoeight before you start taking this medicine and each time you get a refill. There may be new information.

This Patient Product Information does not take the place of talking with your healthcare provider about your medical condition or treatment. If you have questions about Novoeight after reading this information, ask your healthcare provider.

What is the most important information I need to know about Novoeight?

Do not attempt to do an infusion yourself unless you have been taught how by your healthcare provider or hemophilia center.

You must carefully follow your healthcare provider's instructions regarding the dose and schedule for infusing Novoeight so that your treatment will work best for you.

What is Novoeight?

Novoeight is an injectable medicine used to replace clotting factor VIII that is missing in patients with hemophilia A. Hemophilia A is an inherited bleeding disorder that prevents blood from clotting normally.

Novoeight is used to control and prevent bleeding in people with hemophilia A.

Your healthcare provider may give you Novoeight when you have surgery.

Novoeight is not used to treat von Willebrand Disease.

Who should not use Novoeight?

You should not use Novoeight if you

- are allergic to factor VIII or any of the other ingredients of Novoeight
- if you are allergic to hamster proteins

Tell your healthcare provider if you are pregnant or nursing because Novoeight might not be right for you.

What should I tell my healthcare provider before I use Novoeight?

You should tell your healthcare provider if you

- Have or have had any medical conditions.
- Take any medicines, including non-prescription medicines and dietary supplements.
- Are nursing.
- Are pregnant or planning to become pregnant.
- Have been told that you have inhibitors to factor VIII.

How should I use Novoeight?

Treatment with Novoeight should be started by a healthcare provider who is experienced in the care of patients with hemophilia A.

Novoeight is given as an injection into the vein.

You may infuse Novoeight at a hemophilia treatment center, at your healthcare provider's office or in your home. You should be trained on how to do infusions by your hemophilia treatment center or healthcare provider. Many people with hemophilia A learn to infuse the medicine by themselves or with the help of a family member.

Your healthcare provider will tell you how much Novoeight to use based on your weight, the severity of your hemophilia A, and where you are bleeding.

You may need to have blood tests done after getting Novoeight to be sure that your blood level of factor VIII is high enough to clot your blood. This is particularly important if you are having major surgery.

Your healthcare provider will calculate your dose of Novoeight (in international units, IU) depending on your condition and body weight.

Call your healthcare provider right away if your bleeding does not stop after taking Novoeight.

Development of factor VIII inhibitors

Your body can also make antibodies called “inhibitors” against Novoeight, which may stop Novoeight from working properly.

If your bleeding is not adequately controlled, it could be due to the development of factor VIII inhibitors. This should be checked by your healthcare provider. You might need a higher dose of Novoeight or even a different product to control bleeding. Do not increase the total dose of Novoeight to control your bleeding without consulting your healthcare provider.

Use in children

Novoeight can be used in children. Your healthcare provider will decide the dose of Novoeight you will receive.

If you forget to use Novoeight

Do not inject a double dose to make up for a forgotten dose. Proceed with the next injections as scheduled and continue as advised by your healthcare provider.

If you stop using Novoeight

If you stop using Novoeight you are not protected against bleeding. Do not stop using Novoeight without consulting your healthcare provider.

If you have any further questions on the use of this product, ask your healthcare provider.

What if I take too much Novoeight?

Always take Novoeight exactly as your healthcare provider has told you. You should check with your healthcare provider if you are not sure. If you inject more Novoeight than recommended, tell your healthcare provider as soon as possible.

What are the possible side effects of Novoeight?

Common Side Effects Include:

- Inhibitors in patients who were not previously treated with Factor VIII products
- Swelling or itching at the location of injection
- Fever

Other Possible Side Effects:

You could have an allergic reaction to coagulation factor VIII products. Call your healthcare provider right away and stop treatment if you get any of the following signs of an allergic reaction:

- rashes including hives
- difficulty breathing, shortness of breath or wheezing
- tightness of the chest or throat, difficulty swallowing
- swelling of the lips and tongue
- light-headedness, dizziness or loss of consciousness
- pale and cold skin, fast heart beat which may be signs of low blood pressure
- red or swollen face or hands

These are not all of the possible side effects from Novoeight. Ask your healthcare provider for more information. You are encouraged to report side effects to FDA at 1-800-FDA-1088.

Tell your healthcare provider about any side effect that bothers you or that does not go away.

What are the Novoeight dosage strengths?

Novoeight comes in six different dosage strengths. The actual number of international units (IU) of factor VIII in the vial will be imprinted on the label and on the box. The six different strengths are as follows:

Dosage strength of approximately 250 IU per vial

Dosage strength of approximately 500 IU per vial

Dosage strength of approximately 1000 IU per vial

Dosage strength of approximately 1500 IU per vial

Dosage strength of approximately 2000 IU per vial

Dosage strength of approximately 3000 IU per vial

Always check the actual dosage strength printed on the label to make sure you are using the strength prescribed by your doctor.

How should I store Novoeight?

Prior to Reconstitution:

Store in original package in order to protect from light. Do not freeze Novoeight.

Novoeight vials can be stored in the refrigerator (36°F to 46°F [2°C to 8°C]) for up to 30 months or up to the expiration date. During the 30 month shelf life, the product may be kept at room temperature up to 86°F (30°C) for no longer than 12 months, or up to 104°F (40°C) for no longer than 3 months.

If you choose to store Novoeight at room temperature:

- Note the date that the product is removed from refrigeration on the box.
- Do not return the product to the refrigerator.
- Do not use after 12 months if stored up to 86°F (30°C) or after 3 months if stored up to 104°F (40°C) or the expiration date listed on the vial, whichever is earlier.

Do not use this medicine after the expiration date which is on the outer carton and the vial. The expiration date refers to the last day of that month.

After Reconstitution (mixing the dry powder in the vial with the diluent):

The reconstituted Novoeight should appear clear to slightly unclear without particles.

The reconstituted Novoeight should be used immediately.

If you cannot use the Novoeight immediately after it is mixed, it must be used within 4 hours when stored at <86ºF (30°C) or within 2 hours when stored between 86°F (30°C) to 104°F (40°C). Store the reconstituted product in the vial.

Keep this medicine out of the sight and out of reach of children.

What else should I know about Novoeight and hemophilia A?

Medicines are sometimes prescribed for purposes other than those listed here. Do not use Novoeight for a condition for which it is not prescribed. Do not share Novoeight with other people, even if they have the same symptoms that you have.

For more information about Novoeight, please call Novo Nordisk at 1-844-30-EIGHT.

Revised: 07/2020

Novoeight® is a registered trademark of Novo Nordisk Health Care AG.

Patent Information: http://novonordisk-us.com/patients/products/product-patents.html

© 2020 Novo Nordisk

Manufactured by:

Novo Nordisk A/S

DK-2880 Bagsvaerd, Denmark

For information about Novoeight® contact:

Novo Nordisk Inc.

800 Scudders Mill Road

Plainsboro, NJ 08536, USA

Instructions on how to use Novoeight® MixPro®

READ THESE INSTRUCTIONS CAREFULLY BEFORE USING NOVOEIGHT®.

Novoeight® is supplied as a powder. Before injection (administration) it must be mixed (reconstituted) with the liquid diluent supplied in the syringe. The liquid diluent is a sodium chloride solution. The mixed Novoeight® must be injected into your vein (intravenous injection). The equipment in this package is designed to mix and inject Novoeight®.

You will also need an infusion set (tubing and butterfly needle), sterile alcohol swabs, gauze pads, and bandages.

Don’t use the equipment without proper training from your doctor or nurse.

Always wash your hands and ensure that the area around you is clean.

When you prepare and inject medication directly into the veins, it is important to use a clean and germ free (aseptic) technique. Improper technique can introduce germs that can infect the blood.

Don’t open the equipment until you are ready to use it.

Don’t use the equipment if it has been dropped, or if it is damaged. Use a new package instead.

Don’t use the equipment if it is expired. Use a new package instead. The expiration date is printed on the outer carton and on the vial, the vial adapter and the pre-filled syringe.

Don’t use the equipment if you suspect it is contaminated. Use a new package instead.

Don’t dispose of any of the items until after you have injected the mixed solution.

The equipment is for single use only. Single-dose vial. Discard unused portion.

Content

The package contains:

• Vial with Novoeight® powder

• Vial adapter

• Pre-filled syringe with diluent

• Plunger rod (placed under the syringe)

Overview

1. Prepare the vial and the syringe

- Take out the number of Novoeight® packages you need.
- Check the expiry date.
- Check the name and the color of the package, to make sure it contains the correct product.
- Wash your hands and dry them properly using a clean towel or air dry.
- Take the vial, the vial adapter and the pre-filled syringe out of the carton. Leave the plunger rod untouched in the carton.
- Bring the vial and the pre-filled syringe to room temperature. You can do this by holding them in your hands until they feel as warm as your hands.

- Remove the plastic cap from the vial. If the plastic cap is loose or missing, don’t use the vial.
- Wipe the rubber stopper with a sterile alcohol swab and allow it to air dry for a few seconds before use to ensure that it is as germ free as possible.
- Don’t touch the rubber stopper with your fingers as this can transfer germs.

2. Attach the vial adapter

- Remove the protective paper from the vial adapter.
Don’t take the vial adapter out of the protective cap with your fingers. If you touch the spike on the vial adapter germs from your fingers can be transferred.
If the protective paper is not fully sealed or if it is broken, don’t use the vial adapter.

- Place the vial on a flat and solid surface.
- Turn over the protective cap, and snap the vial adapter onto the vial.
Once attached, don’t remove the vial adapter from the vial.

- Lightly squeeze the protective cap with your thumb and index finger as shown. Remove the protective cap from the vial adapter.
Don’t lift the vial adapter from the vial when removing the protective cap.

3. Attach the plunger rod and the syringe

- Grasp the plunger rod by the wide top end and take it out of the carton. Don’t touch the sides or the thread of the plunger rod. If you touch the sides or the thread germs from your fingers can be transferred.
- Immediately connect the plunger rod to the syringe by turning it clockwise into the rubber plunger inside the pre-filled syringe until resistance is felt.

- Remove the syringe cap from the pre-filled syringe by bending it down until the perforation breaks.
Don’t touch the syringe tip under the syringe cap. If you touch the syringe tip germs from your fingers can be transferred.
If the syringe cap is loose or missing, don’t use the pre-filled syringe.

- Screw the pre-filled syringe securely onto the vial adapter until resistance is felt.

4. Mix the powder with the diluent

- Hold the pre-filled syringe slightly tilted with the vial pointing downwards.
- Push the plunger rod to inject all the diluent into the vial.

- Keep the plunger rod pressed down and swirl the vial gently until all the powder is dissolved.
Don’t shake the vial as this will cause foaming.
- Check the mixed solution. It must be clear to slightly opalescent (slightly unclear). If you notice visible particles or discoloration, don’t use it. Use a new package instead.

Novoeight® is recommended to be used immediately after it is mixed. This is because if left, the medicine may no longer be sterile and could cause infections.

If you cannot use the mixed Novoeight® solution immediately, it must be used within 4 hours when stored at <86ºF (30°C) or within 2 hours when stored between 86ºF (30ºC) to 104ºF (40ºC). Store the reconstituted product in the vial.

Do not freeze mixed Novoeight® solution or store it in syringes.

Keep mixed Novoeight® solution out of direct light.

If your dose requires more than one vial, repeat step A to J with additional vials, vial adapters and pre-filled syringes until you have reached your required dose.

- Keep the plunger rod pushed completely in.
- Turn the syringe with the vial upside down.
- Stop pushing the plunger rod and let it move back on its own while the mixed solution fills the syringe.
- Pull the plunger rod slightly downwards to draw the mixed solution into the syringe.
- In case you only need part of the entire vial, use the scale on the syringe to see how much mixed solution you withdraw, as instructed by your doctor or nurse.
- While holding the vial upside down, tap the syringe gently to let any air bubbles rise to the top.
- Push the plunger rod slowly until all air bubbles are gone.

- Unscrew the vial adapter with the vial.

Don’t touch the syringe tip. If you touch the syringe tip germs from your fingers can be transferred.

Caution: The pre-filled diluent syringe is made of glass with an internal tip diameter of 0.037 inches, and is compatible with a standard Luer-lock connector.

Some needleless connectors for intravenous catheters are incompatible with the glass diluent syringes (for example, certain connectors with an internal spike, such as Clave® /MicroClave®, InVision-Plus®, InVision-Plus CS®, Invision-Plus Junior®, Bionector®).

The use of these needleless connectors can damage the connector and affect administration.

To administer Novoeight through incompatible needleless connectors, withdraw reconstituted product into a standard 10 mL sterile Luer-lock plastic syringe.

If you have encountered any problems with attaching the pre-filled sodium chloride diluent syringe to any Luer- lock compatible device, please contact Novo Nordisk at (844) 303-4448.

5. Inject the mixed solution

Novoeight® is now ready to inject into your vein.

- Do not mix Novoeight® with any other intravenous infusions or medications.
- Inject the mixed solution slowly over 2 to 5 minutes as instructed by your doctor or nurse.

Injecting the solution via a central venous access device (CVAD) such as a central venous catheter or subcutaneous port:

- Use a clean and germ free (aseptic) technique. Follow the instructions for proper use for your connector and central venous access device in consultation with your doctor or nurse.
- Injecting into a CVAD may require using a sterile 10 mL plastic syringe for withdrawal of the mixed solution and injection.
- If necessary, use 0.9% Sodium Chloride Injection, USP to flush the CVAD line before or after Novoeight® injection.

The peel-off label found on the Novoeight® vial can be used to record the lot number.

Disposal

- After injection, safely dispose of all unused Novoeight® solution, the syringe with the infusion set, the vial with the vial adapter, and other waste materials in an appropriate container for throwing away medical waste.
Don’t throw it out with the ordinary household trash.

Don’t disassemble the vial and vial adapter before disposal.

Don’t reuse the equipment.

Important information

Contact your healthcare provider or local hemophilia treatment center if you experience any problems.

For full Prescribing Information please read the other insert included in this package.

Novoeight® and MixPro® are registered trademarks of Novo Nordisk Health Care AG.

Patent Information: http://novonordisk-us.com/patients/products/product-patents.html

Clave® and MicroClave® are registered trademarks of ICU Medical Inc.

InVision-Plus®, InVision-Plus CS®, Invision-Plus®Junior® are registered trademarks of RyMed Technologies, Inc.

Bionector® is a registered trademark of Vygon

© 2020 Novo Nordisk

Manufactured by:

Novo Nordisk A/S

DK-2880 Bagsvaerd, Denmark

For information about Novoeight® contact:

Novo Nordisk Inc.

800 Scudders Mill Road

Plainsboro, NJ 08536, USA

License No: 1261

Revised: 07/2020

Principal Display Panel

250 IU Carton

NDC 0169 7825 01 List: 782501

Novoeight®

Antihemophilic Factor (Recombinant)

250 IU

Intravenous use, after reconstitution

Single dose. Discard unused portion.

Contains no preservatives

Rx Only

Includes MixPro®

a vial adapter and pre-filled diluent syringe

500 IU Carton

NDC 0169 7850 01 List: 785001

Novoeight®

Antihemophilic Factor (Recombinant)

500 IU

Intravenous use, after reconstitution

Single dose. Discard unused portion.

Contains no preservatives

Rx Only

Includes MixPro®

a vial adapter and pre-filled diluent syringe

1000 IU Carton

NDC 0169 7810 01 List: 781001

Novoeight®

Antihemophilic Factor (Recombinant)

1000 IU

Intravenous use, after reconstitution

Single dose. Discard unused portion.

Contains no preservatives

Rx Only

Includes MixPro®

a vial adapter and pre-filled diluent syringe

1500 IU Carton

NDC 0169 7815 01 List: 781501

Novoeight®

Antihemophilic Factor (Recombinant)

1500 IU

Intravenous use, after reconstitution

Single dose. Discard unused portion.

Contains no preservatives

Rx Only

Includes MixPro®

a vial adapter and pre-filled diluent syringe

2000 IU Carton

NDC 0169 7820 01 List: 782001

Novoeight®

Antihemophilic Factor (Recombinant)

2000 IU

Intravenous use, after reconstitution

Single dose. Discard unused portion.

Contains no preservatives

Rx Only

Includes MixPro®

a vial adapter and pre-filled diluent syringe

3000 IU Carton

NDC 0169 7830 01 List: 783001

Novoeight®

Antihemophilic Factor (Recombinant)

3000 IU

Intravenous use, after reconstitution

Single dose. Discard unused portion.

Contains no preservatives

Rx Only

Includes MixPro®

a vial adapter and pre-filled diluent syringe

250 IU Vial Label

NDC 0169 7829 11

Novoeight®

Antihemophilic Factor

(Recombinant)

Store in a refrigerator 36°F -

46°F (2-8°C)

500 IU Vial Label

NDC 0169 7851 11

Novoeight®

Antihemophilic Factor

(Recombinant)

Store in a refrigerator 36°F -

46°F (2-8°C)

1000 IU Vial Label

NDC 0169 7811 11

Novoeight®

Antihemophilic Factor

(Recombinant)

Store in a refrigerator 36°F -

46°F (2-8°C)

1500 IU Vial Label

NDC 0169 7855 11

Novoeight®

Antihemophilic Factor

(Recombinant)

Store in a refrigerator 36°F -

46°F (2-8°C)

2000 IU Vial Label

NDC 0169 7821 11

Novoeight®

Antihemophilic Factor

(Recombinant)

Store in a refrigerator 36°F -

46°F (2-8°C)

3000 IU Vial Label

NDC 0169 7831 11

Novoeight®

Antihemophilic Factor

(Recombinant)

Store in a refrigerator 36°F -

46°F (2-8°C)

Syringe Label

NDC 0169 7008 98

Sodium Chloride Solution

For reconstitution of Novoeight®

Store in a refrigerator 36°F to 46°F (2°C to 8°C)

Do not freeze

Rx Only

Single Use Only